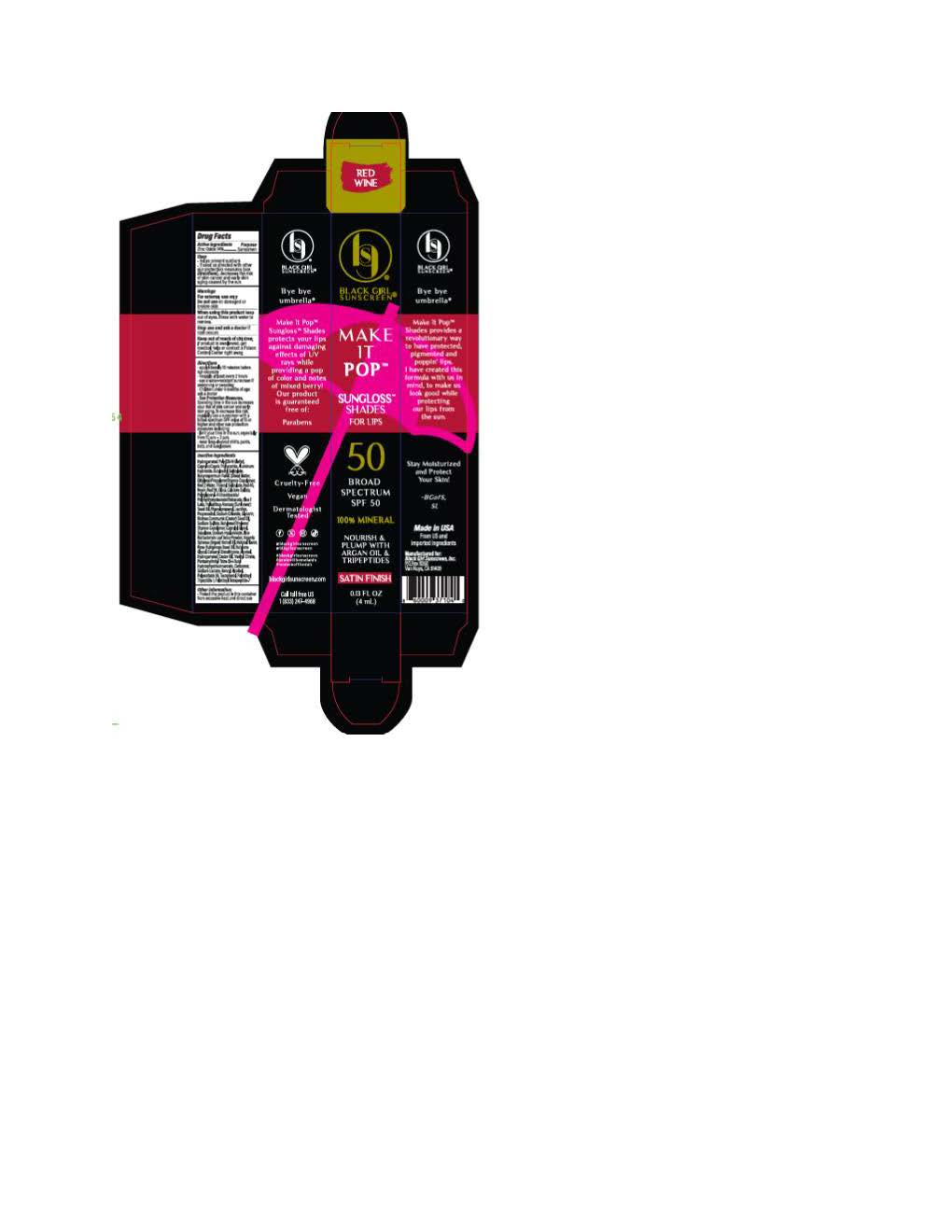 DRUG LABEL: Black Girl Sunscreen Make It Pop
NDC: 84204-2261 | Form: LOTION
Manufacturer: Black Girl Sunscreen
Category: otc | Type: HUMAN OTC DRUG LABEL
Date: 20251009

ACTIVE INGREDIENTS: ZINC OXIDE 154 mg/1 mL
INACTIVE INGREDIENTS: ALCOHOL; HYDROGENATED POLY(C6-14 OLEFIN; 2 CST); TRIDECYL SALICYLATE; SODIUM SULFATE; ARGANIA SPINOSA KERNEL OIL; BUTYLENE GLYCOL; HELIANTHUS ANNUUS (SUNFLOWER) SEED OIL; HYDROGENATED CASTOR OIL; CARBOMER; SODIUM LACTATE; POLYSORBATE 20; SODIUM HYALURONATE; TRIETHYL CITRATE; ALUMINUM HYDROXIDE; TOCOPHEROL; D&C RED NO. 7; SODIUM CHLORIDE; SILICON DIOXIDE; FERRIC OXIDE YELLOW; FERROSOFERRIC OXIDE; LECITHIN, SOYBEAN; SQUALANE; BUTYLOCTYL SALICYLATE; PHENYLPROPANOL; PENTAERYTHRITYL TETRA-DI-T-BUTYL HYDROXYHYDROCINNAMATE; FERRIC OXIDE RED; ALKYL (C12-15) BENZOATE; CAPRYLIC/CAPRIC TRIGLYCERIDE; CAPRYLYL GLYCOL; POLYGLYCERYL-4 DIISOSTEARATE/POLYHYDROXYSTEARATE/SEBACATE; WATER; CALCIUM SULFATE; BUTYROSPERMUM PARKII (SHEA) BUTTER; ROSIN; PROPANEDIOL; RICINUS COMMUNIS (CASTOR) SEED OIL; PALMITOYL TRIPEPTIDE-1; ROSA RUBIGINOSA SEED OIL; PALMITOYL TETRAPEPTIDE-7; BLUE 1 LAKE; RED 28; GLYCERIN

Black Girl Sunscreen Make It Pop